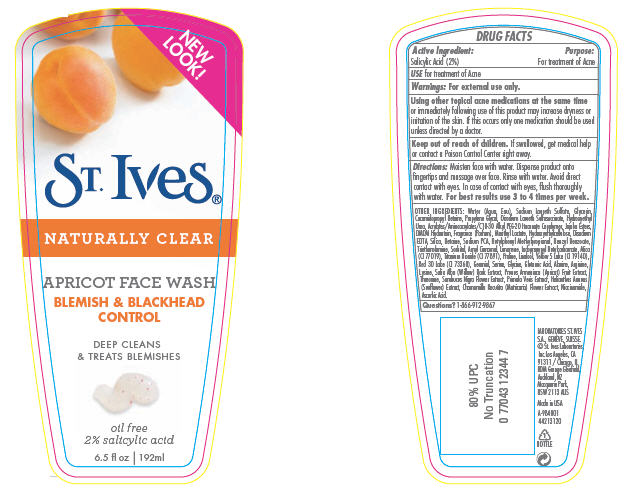 DRUG LABEL: St. Ives Blemish and Blackhead Facial
NDC: 12488-0200 | Form: SOAP
Manufacturer: Alberto-Culver USA Inc.
Category: otc | Type: HUMAN OTC DRUG LABEL
Date: 20091217

ACTIVE INGREDIENTS: Salicylic Acid 0.02 mL/1 mL
INACTIVE INGREDIENTS: Water; Edetate Disodium; Sodium Laureth Sulfate; Glycerin; Cocamidopropyl Betaine; Trolamine; Primula Veris; Iodopropynyl Butylcarbamate; Betaine; Sodium Pyrrolidone Carboxylate; Sorbitol; Serine; Glycine; Glutamic Acid; Lysine; Alanine; Arginine; Threonine; Proline; Disodium Laureth Sulfosuccinate; Silicon Dioxide; Titanium Dioxide; Niacinamide; Propylene Glycol; Ascorbic Acid

St. Ives®
NATURALLY CLEAR
APRICOT FACE WASH

DRUG FACTS

Active Ingredient

Salicylic Acid (2%)

Purpose

For treatment of Acne

INDICATIONS AND USAGE

USE for treatment of Acne

Warnings

For external use only.

WHEN USING

Using other topical acne medications at the same time or immediately following use of this product may increase dryness or irritation of the skin. If this occurs only one medication should be used unless directed by a doctor.

Keep out of reach of children. If swallowed, get medical help or contact a Poison Control Center right away.

Directions

Moisten face with water. Dispense product onto fingertips and massage over face. Rinse with water. Avoid direct contact with eyes. In case of contact with eyes, flush thoroughly with water. For best results use 3 to 4 times per week.

OTHER INGREDIENTS

Water (Aqua, Eau), Sodium Laureth Sulfate, Glycerin, Cocamidopropyl Betaine, Propylene Glycol, Disodium Laureth Sulfosuccinate, Hydroxyethyl Urea, Acrylates/Aminoacrylates/C10-30 Alkyl PEG-20 Itaconate Copolymer, Jojoba Esters, DMDM Hydantoin, Fragrance (Parfum), Menthyl Lactate, Hydroxyethylcellulose, Disodium EDTA, Silica, Betaine, Sodium PCA, Butylphenyl Methylpropional, Benzyl Benzoate, Triethanolamine, Sorbitol, Amyl Cinnamal, Limonene, Iodopropynyl Butylcarbamate, Mica (CI 77019), Titanium Dioxide (CI 77891), Proline, Linalool, Yellow 5 Lake (CI 19140), Red 30 Lake (CI 73360), Geraniol, Serine, Glycine, Glutamic Acid, Alanine, Arginine, Lysine, Salix Alba (Willow) Bark Extract, Prunus Armeniaca (Apricot) Fruit Extract, Threonine, Sambucus Nigra Flower Extract, Primula Veris Extract, Helianthus Annuus (Sunflower) Extract, Chamomilla Recutita (Matricaria) Flower Extract, Niacinamide, Ascorbic Acid.

Questions?

1-866-912-9867

PRINCIPAL DISPLAY PANEL - 170g Tube

NEW
LOOK!

St. Ives®

NATURALLY CLEAR

APRICOT FACE WASH

BLEMISH & BLACKHEAD
CONTROL

DEEP CLEANS
& TREATS BLEMISHES

oil free
2% salicylic acid

6.5 fl oz / 192ml